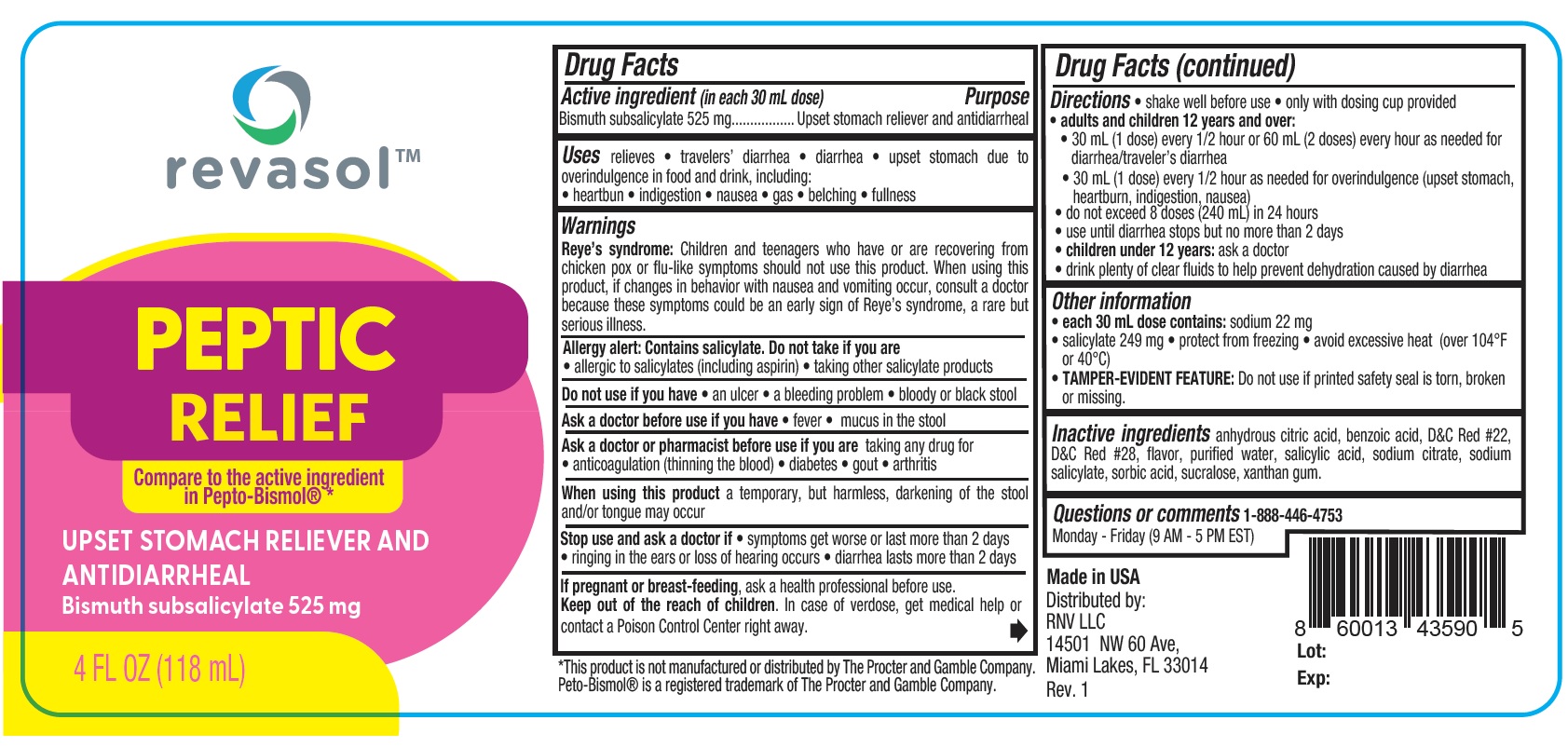 DRUG LABEL: Revasol Peptic Relief
NDC: 84379-283 | Form: LIQUID
Manufacturer: Rnv LLC
Category: otc | Type: HUMAN OTC DRUG LABEL
Date: 20250321

ACTIVE INGREDIENTS: BISMUTH SUBSALICYLATE 525 mg/30 mL
INACTIVE INGREDIENTS: ANHYDROUS CITRIC ACID; SALICYLIC ACID; XANTHAN GUM; METHYL SALICYLATE; WATER; SODIUM SALICYLATE; SUCRALOSE; SODIUM CITRATE; SORBIC ACID; D&C RED NO. 22; D&C RED NO. 28; BENZOIC ACID

REVASOL PEPTIC RELIEF

Active ingredient (in each 30 mL dose) Purpose

Bismuth subsalicylate 525 mg...................Upset stomach reliever and antidiarrheal

PURPOSE

Upset stomach reliever and antidiarrheal

Uses

relieves • travelers’ diarrhea • diarrhea • upset stomach due to overindulgence in food and drink, including:
• heartbun • indigestion • nausea • gas • belching • fullness

Warnings

Reye’s syndrome: Children and teenagers who have or are recovering from
chicken pox or flu-like symptoms should not use this product. When using this
product, if changes in behavior with nausea and vomiting occur, consult a doctor
because these symptoms could be an early sign of Reye’s syndrome, a rare but
serious illness.

Allergy alert: Contains salicylate. Do not take if you are
• allergic to salicylates (including aspirin) • taking other salicylate products

Do not use if you have • an ulcer • a bleeding problem • bloody or black stool

Ask a doctor before use if you have • fever • mucus in the stool

Ask a doctor or pharmacist before use if you are taking any drug for
• anticoagulation (thinning the blood) • diabetes • gout • arthritis

When using this product a temporary, but harmless, darkening of the stool
and/or tongue may occur

Stop use and ask a doctor if • symptoms get worse or last more than 2 days
• ringing in the ears or loss of hearing occurs • diarrhea lasts more than 2 days

PREGNANCY OR BREAST FEEDING

If pregnant or breast-feeding, ask a health professional before use.

KEEP OUT OF REACH OF CHILDREN

Keep out of the reach of children. In case of overdose, get medical help or
contact a Poison Control Center right away.

Directions

• shake well before use • only with dosing cup provided

• adults and children 12 years and over:

• 30 mL (1 dose) every 1/2 hour or 60 mL (2 doses) every hour as needed for
diarrhea/traveler’s diarrhea

• 30 mL (1 dose) every 1/2 hour as needed for overindulgence (upset stomach,
heartburn, indigestion, nausea)

• do not exceed 8 doses (240 mL) in 24 hours

• use until diarrhea stops but no more than 2 days
• children under 12 years: ask a doctor
• drink plenty of clear fluids to help prevent dehydration caused by diarrhea

Other information
• each 30 mL dose contains: sodium 22 mg
• salicylate 249 mg • protect from freezing • avoid excessive heat (over 104°F
or 40°C)
• TAMPER-EVIDENT FEATURE: Do not use if printed safety seal is torn, broken
or missing.

Inactive ingredients

anhydrous citric acid, benzoic acid, D&C Red #22,
D&C Red #28, flavor, purified water, salicylic acid, sodium citrate, sodium
salicylate, sorbic acid, sucralose, xanthan gum.

Questions or comments 1-888-446-4753
Monday - Friday (9 AM - 5 PM EST)